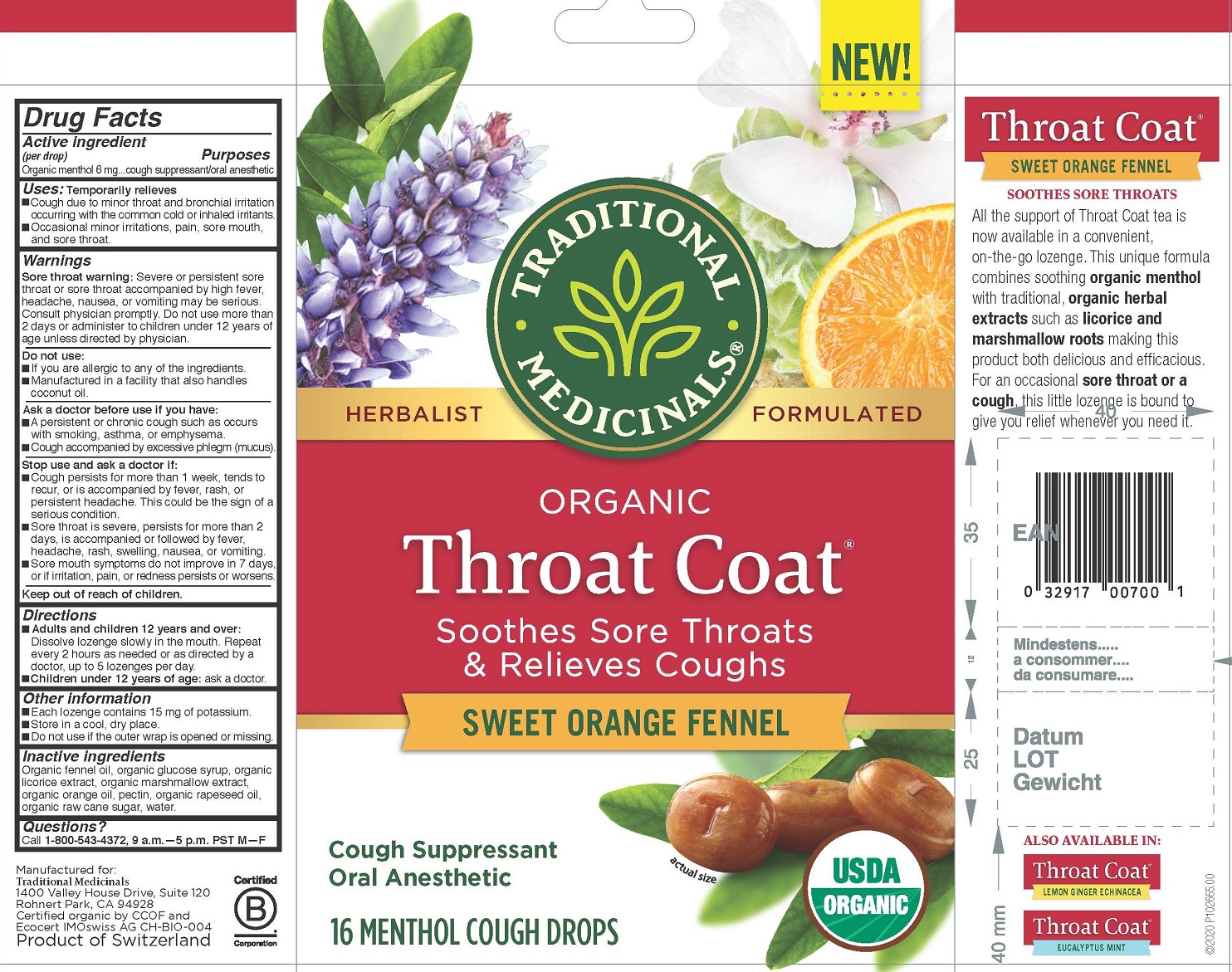 DRUG LABEL: Throat Coat
NDC: 78732-001 | Form: LOZENGE
Manufacturer: Traditional Medicinals, Inc.
Category: otc | Type: HUMAN OTC DRUG LABEL
Date: 20251205

ACTIVE INGREDIENTS: MENTHOL, UNSPECIFIED FORM 6 mg/4.2 g
INACTIVE INGREDIENTS: WATER; LICORICE; PECTIN; ALTHAEA OFFICINALIS ROOT; FENNEL OIL; CANOLA OIL; RAW SUGAR; ORANGE OIL; CORN SYRUP

Organic Throat Coat - Sweet Orange Fennel 6 mg

Active ingredient

Active ingredient (per drop) Organic menthol 6 mg

Purpose

Purposes cough suppressant / oral anesthetic

Uses

Temporarily relieves

- Cough due to minor throat and bronchial irritation occurring with the common cold and inhaled irritants.
- Occasional minor irritaions, pain, sore mouth, and sore throat.

Warnings

Sore throat warning: Severe or persistent sore throat or sore throat accompanied by high fever, headache, nausea, or vomiting may be serious. Consult physician promptly. Do not use more than 2 days or administer to children under 12 years of age unless directed by physician.

Do not use

- If you are allergic to any of the ingredients.
- Manufactured in a facility that also handles coconut oil

Ask a doctor before use if you have:

- A persistent or chronic cough such as occurs with smoking, asthma, or emphysema.
- Cough accopanied by excessive phlegm (mucus)

Stop use and ask a doctor if:

- Cough persists for more than 1 week, tends to recur, or is accompanied by fever, rash, or persistent heacache. This could be the sign of a sereious condition.
- Sore throat is severe, persists for more than 2 days, is accompanied or followed by fever, headache, rash, swelling, nausea or vomiting.
- Sore mouth symptoms do not improve in 7 days, or if irritation, pain, or redness persistst or worsesns.

Keep out of reach of children

Directions

- Adults and children 12 years and over: Dissolve lozenge slowly in the mouth. Repeat every 2 hours as needed or as directed by a doctor, up to 5 lozenges per day
- Children under 12 years of age: ask a doctor.

Other information

- Each lozenge contains 15 mg of potassium.
- Store in a cool, dry place.
- Do not use if the outer wrap is opened or missing.

Inactive ingredients

Organic fennel oil, organic glucose syrup, organic licorice extract, organic marshmallow extract, organic orange oil, pectin, organic rapeseed oil, organic raw cane sugar, water.

Questions

call 1-800-543-4372, 9 a.m. - 5 p.m. PST M-F

TRADITIONAL MEDICINALS®

ORGANIC Throat Coat®

Soothes Sore Throats & Relieves Coughs

SWEET ORANGE FENNEL

Cough Suppressant

Oral Anesthetic

16 MENTHOL COUGH DROPS

Manufactured for:

Traditional Medicinals

1400 Valley House Dr, Suite 120

Rohnert Park, CA 94928

Product of Switzerland